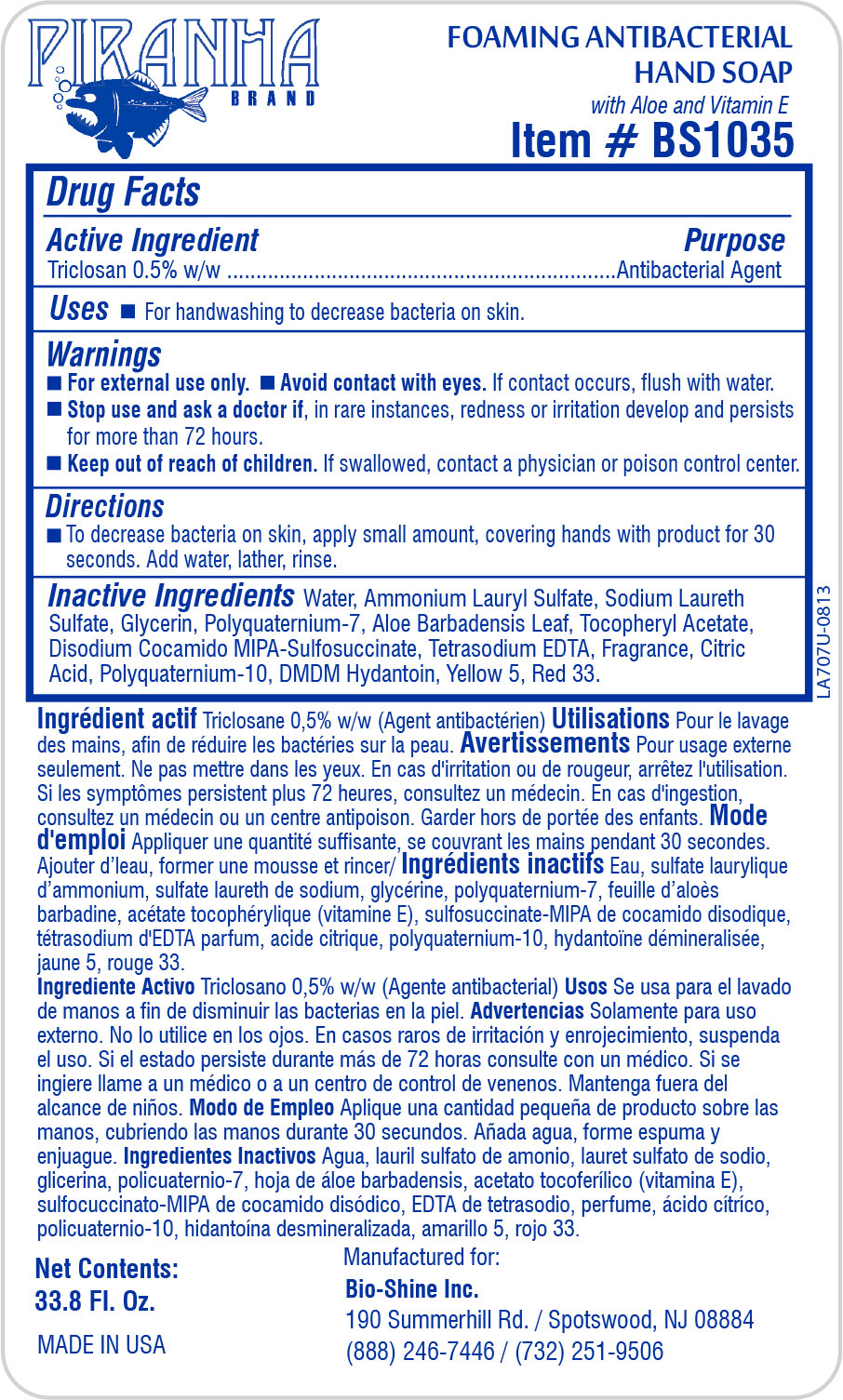 DRUG LABEL: Piranha Brand Foaming Antibacterial Hand
NDC: 61625-689 | Form: SOLUTION
Manufacturer: Bio Shine, Inc.
Category: otc | Type: HUMAN OTC DRUG LABEL
Date: 20140311

ACTIVE INGREDIENTS: TRICLOSAN 18.9 g/100 mL
INACTIVE INGREDIENTS: WATER; POLYQUATERNIUM-10 (1000 MPA.S AT 2%); EDETATE SODIUM; AMMONIUM LAURYL SULFATE; SODIUM LAURETH SULFATE; POLYQUATERNIUM-7 (70/30 ACRYLAMIDE/DADMAC; 1600 KD); GLYCERIN; ANHYDROUS CITRIC ACID; DMDM HYDANTOIN; ALOE VERA LEAF; ALPHA-TOCOPHEROL ACETATE; D&C RED NO. 33; FD&C YELLOW NO. 5; ISOSTEARAMIDOPROPYL MORPHOLINE LACTATE

Piranha Brand Foaming Antibacterial Hand

ACTIVE INGREDIENT

Triclosan 0.5% w/w.......Antibacterial Agent

INACTIVE INGREDIENT

Water, Ammonium Lauryl Sulfate, Sodium Laureth Sulfate, Glycerin, Polyquaternium-7, Aloe Barbadensis Leaf, Tocopheryl Acetate, Disodium Cocamido MIPA-Sulfosuccinate, Tetrasodium EDTA, Fragance, Citric Acid, Polyquaternium-10, DMDM Hydantoin, Yellow 5, Red 33.

Keep out of reach of children. If swallowed, contact a physician or poison control center.

WARNINGS

For external use only.

Avoid contact with eyes. If contact occurs, flush with water.

Stop use and ask a doctor if, in rare instances, redness or irritation develop and persists for more than 72 hours.

Keep out of reach of children. If swallowed, contact a physician or poison control center.

PURPOSE

For handwashing to decrease bacteria on skin.

DOSAGE AND ADMINISTRATION

To decrease bacteria on skin, apply small amount, covering hands with product for 30 seconds. Add water, lather, rinse.

INDICATIONS AND USAGE

For handwashing to decrease bacteria on skin.

Avoid contact with eyes. If contact occurs, flush with water.

Stop use and ask a doctor if, in rare instances, redness or irritation develop and persists for more than 72 hours.

Keep out of reach of children. If swallowed, contact a physician or poison control center.

PACKAGE LABEL

61625-689-41.jpg